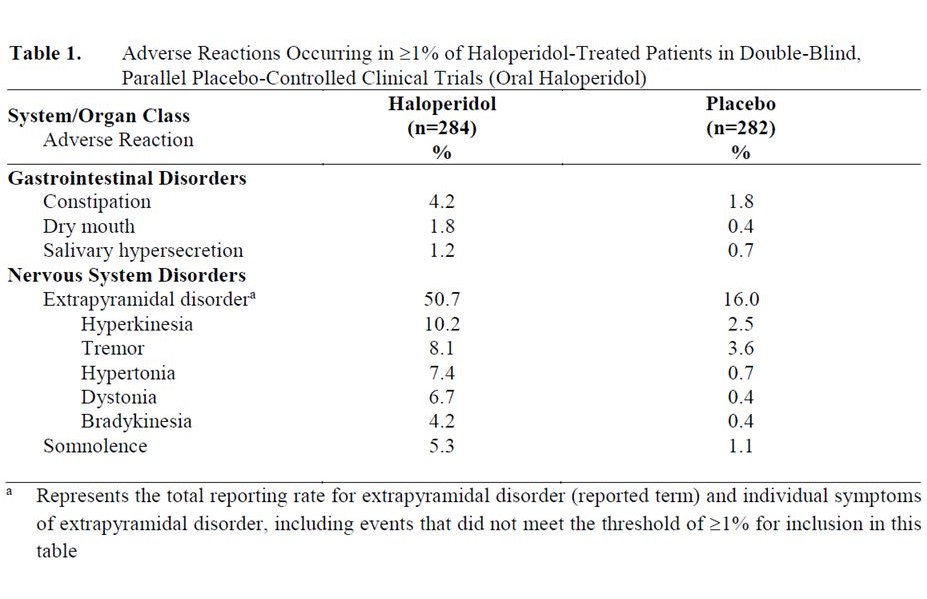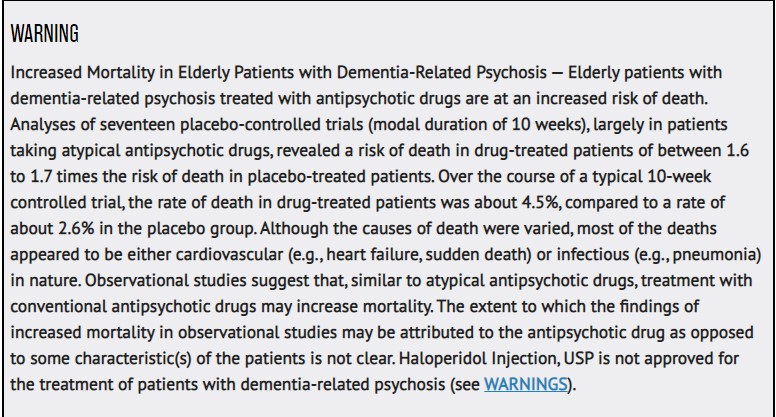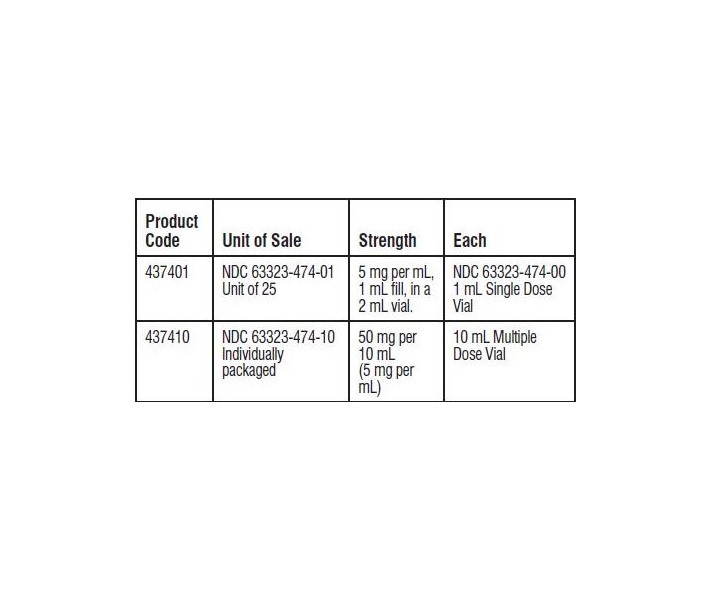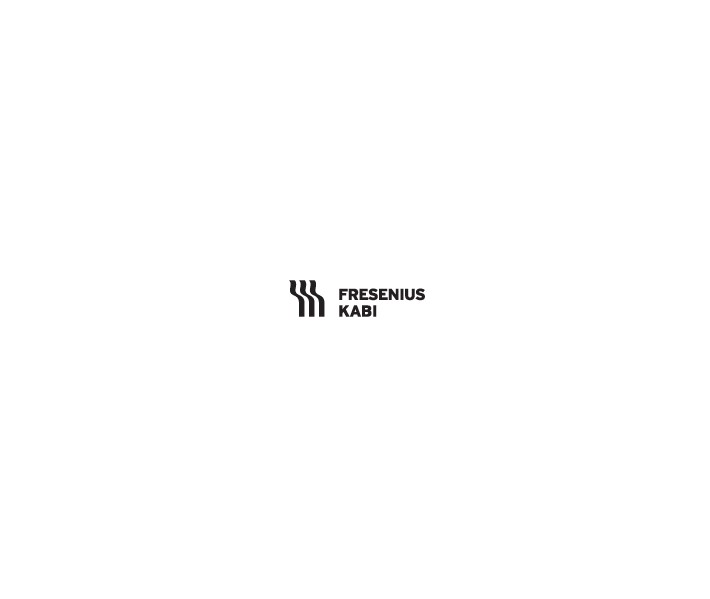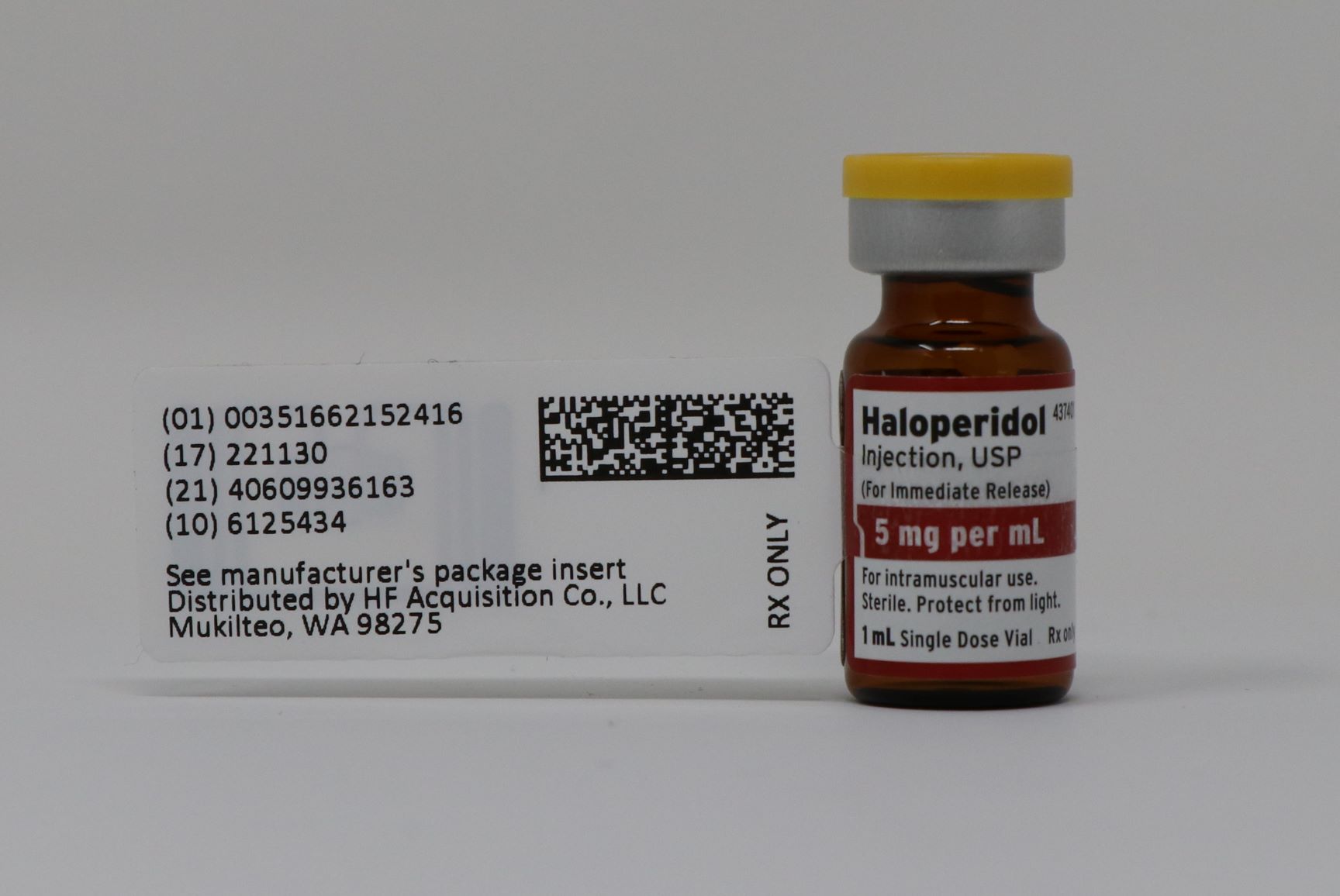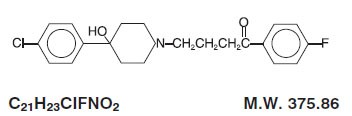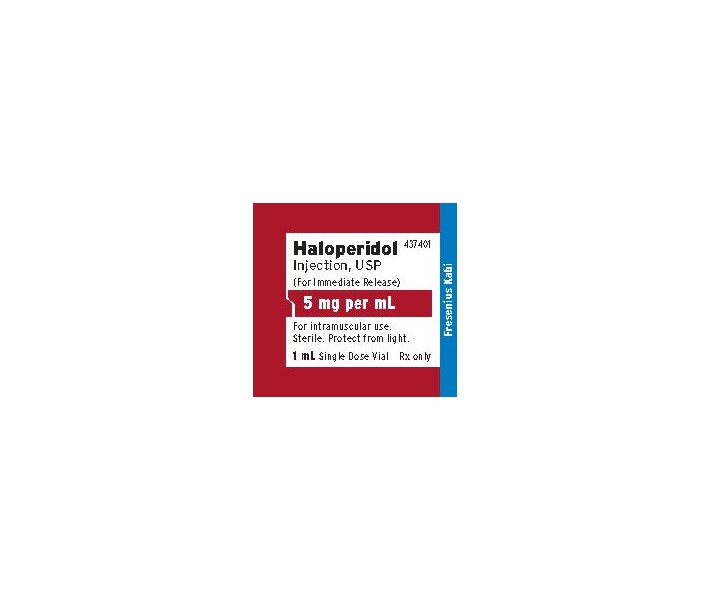 DRUG LABEL: HALOPERIDOL
NDC: 51662-1524 | Form: INJECTION, SOLUTION
Manufacturer: HF Acquisition Co LLC, DBA HealthFirst
Category: prescription | Type: HUMAN PRESCRIPTION DRUG LABEL
Date: 20210329

ACTIVE INGREDIENTS: HALOPERIDOL LACTATE 5 mg/1 mL
INACTIVE INGREDIENTS: PROPYLPARABEN 0.2 mg/1 mL; METHYLPARABEN 1.8 mg/1 mL; LACTIC ACID

HALOPERIDOL INJECTION, USP (FOR IMMEDIATE RELEASE) 5 mg PER mL 1mL VIAL

SPL UNCLASSIFIED

Rx only

(For Immediate Release)

DESCRIPTION

Haloperidol is the first of the butyrophenone series of major antipsychotics. The chemical designation is 4-[4-(p-chlorophenyl)-4-hydroxypiperidino]- 4’-fluorobutyrophenone and it has the following structural formula:

Haloperidol Injection, USP is available as a sterile parenteral form for intramuscular injection. The injection provides 5 mg haloperidol (as the lactate) with 1.8 mg methylparaben and 0.2 mg propylparaben per mL, and lactic acid for pH adjustment between 3.0 to 3.8.

ACTIONS

The precise mechanism of action has not been clearly established.

INDICATIONS

Haloperidol injection is indicated for use in the treatment of schizophrenia.

Haloperidol is indicated for the control of tics and vocal utterances of Tourette's Disorder.

CONTRAINDICATIONS

Haloperidol injection is contraindicated in severe toxic central nervous system depression or comatose states from any cause and in individuals who are hypersensitive to this drug or have Parkinson’s disease.

WARNINGS

Increased Mortality in Elderly Patients with Dementia-Related Psychosis

Elderly patients with dementia-related psychosis treated with antipsychotic drugs are at an increased risk of death. Haloperidol injection is not approved for the treatment of patients with dementia-related psychosis (see BOXED WARNING).

Cardiovascular Effects

Cases of sudden death, QT-prolongation, and Torsades de Pointes have been reported in patients receiving haloperidol injection. Higher than recommended doses of any formulation and intravenous administration of haloperidol injection appear to be associated with a higher risk of QT-prolongation and Torsades de Pointes. Although cases have been reported even in the absence of predisposing factors, particular caution is advised in treating patients with other QT-prolonging conditions (including electrolyte imbalance [particularly hypokalemia and hypomagnesemia], drugs known to prolong QT, underlying cardiac abnormalities, hypothyroidism, and familial long QT-syndrome). HALOPERIDOL INJECTION IS NOT APPROVED FOR INTRAVENOUS ADMINISTRATION. If haloperidol injection is administered intravenously, the ECG should be monitored for QT-prolongation and arrhythmias.

Tardive Dyskinesia

A syndrome consisting of potentially irreversible, involuntary, dyskinetic movements may develop in patients treated with antipsychotic drugs (see ADVERSE REACTIONS). Although the prevalence of the syndrome appears to be highest among the elderly, especially elderly women, it is impossible to rely upon prevalence estimates to predict, at the inception of antipsychotic treatment, which patients are likely to develop the syndrome. Whether antipsychotic drug products differ in their potential to cause tardive dyskinesia is unknown.

Both the risk of developing tardive dyskinesia and the likelihood that it will become irreversible are believed to increase as the duration of treatment and the total cumulative dose of antipsychotic drugs administered to the patient increase. However, the syndrome can develop, although much less commonly, after relatively brief treatment periods at low doses.

There is no known treatment for established cases of tardive dyskinesia, although the syndrome may remit, partially or completely, if antipsychotic treatment is withdrawn. Antipsychotic treatment, itself, however, may suppress (or partially suppress) the signs and symptoms of the syndrome and thereby may possibly mask the underlying process. The effect that symptomatic suppression has upon the long-term course of the syndrome is unknown.

Given these considerations, antipsychotic drugs should be prescribed in a manner that is most likely to minimize the occurrence of tardive dyskinesia. Chronic antipsychotic treatment should generally be reserved for patients who suffer from a chronic illness that, 1) is known to respond to antipsychotic drugs, and, 2) for whom alternative, equally effective, but potentially less harmful treatments are not available or appropriate. In patients who do require chronic treatment, the smallest dose and the shortest duration of treatment producing a satisfactory clinical response should be sought. The need for continued treatment should be reassessed periodically.

If signs and symptoms of tardive dyskinesia appear in a patient on antipsychotics, drug discontinuation should be considered. However, some patients may require treatment despite the presence of the syndrome.

Neuroleptic Malignant Syndrome (NMS)

A potentially fatal symptom complex sometimes referred to as Neuroleptic Malignant Syndrome (NMS) has been reported in association with antipsychotic drugs (see ADVERSE REACTIONS). Clinical manifestations of NMS are hyperpyrexia, muscle rigidity, altered mental status (including catatonic signs) and evidence of autonomic instability (irregular pulse or blood pressure, tachycardia, diaphoresis, and cardiac dysrhythmias). Additional signs may include elevated creatine phosphokinase, myoglobinuria (rhabdomyolysis) and acute renal failure.
The diagnostic evaluation of patients with this syndrome is complicated. In arriving at a diagnosis, it is important to identify cases where the clinical presentation includes both serious medical illness (e.g., pneumonia, systemic infection, etc.) and untreated or inadequately treated extrapyramidal signs and symptoms. Other important considerations in the differential diagnosis include central anticholinergic toxicity, heat stroke, drug fever and primary central nervous system (CNS) pathology.
The management of NMS should include 1) immediate discontinuation of antipsychotic drugs and other drugs not essential to concurrent therapy, 2) intensive symptomatic treatment and medical monitoring, and 3) treatment of any concomitant serious medical problems for which specific treatments are available. There is no general agreement about specific pharmacological treatment regimens for uncomplicated NMS.
If a patient requires antipsychotic drug treatment after recovery from NMS, the potential reintroduction of drug therapy should be carefully considered. The patient should be carefully monitored, since recurrences of NMS have been reported.
Hyperpyrexia and heat stroke, not associated with the above symptom complex, have also been reported with haloperidol.

Treatment Withdrawal

Generally, patients receiving short-term therapy experience no problems with abrupt discontinuation of antipsychotic drugs. However, some patients on maintenance treatment experience transient dyskinetic signs after abrupt withdrawal. In certain of these cases the dyskinetic movements are indistinguishable from tardive dyskinesia (see WARNINGS, TARDIVE DYSKINESIA) except for duration. It is not known whether gradual withdrawal of antipsychotic drugs will reduce the rate of occurrence of withdrawal emergent neurological signs but until further evidence becomes available, it seems reasonable to gradually withdraw use of Haloperidol injection (see WARNINGS, USAGE IN PREGNANCY).

Falls

Motor instability, somnolence, and orthostatic hypotension have been reported with the use of antipsychotics, including haloperidol, which may lead to falls and, consequently, fractures or other fall-related injuries. For patients, particularly the elderly, with diseases, conditions, or medications that could exacerbate these effects, assess the risk of falls when initiating antipsychotic treatment and recurrently for patients receiving repeated doses.

Usage in Pregnancy

Rodents given 2 to 20 times the usual maximum human dose of haloperidol by oral or parenteral routes showed an increase in incidence of resorption, reduced fertility, delayed delivery and pup mortality. No teratogenic effect has been reported in rats, rabbits or dogs at dosages within this range, but cleft palate has been observed in mice given 15 times the usual maximum human dose. Cleft palate in mice appears to be a nonspecific response to stress or nutritional imbalance as well as to a variety of drugs, and there is no evidence to relate this phenomenon to predictable human risk for most of these agents.

There are no well controlled studies with haloperidol injection in pregnant women. There are reports, however, of cases of limb malformations observed following maternal use of haloperidol along with other drugs which have suspected teratogenic potential during the first trimester of pregnancy. Causal relationships were not established in these cases. Since such experience does not exclude the possibility of fetal damage due to haloperidol, this drug should be used during pregnancy or in women likely to become pregnant only if the benefit clearly justifies a potential risk to the fetus. Infants should not be nursed during drug treatment.

Non-Teratogenic Effects

Neonates exposed to antipsychotic drugs (including haloperidol) during the third trimester of pregnancy are at risk for extrapyramidal and/or withdrawal symptoms following delivery. There have been reports of agitation, hypertonia, hypotonia, tremor, somnolence, respiratory distress, and feeding disorder in these neonates. These complications have varied in severity; while in some cases symptoms have been self-limited, in other cases neonates have required intensive care unit support and prolonged hospitalization.

Haloperidol should be used during pregnancy only if the potential benefit justifies the potential risk to the fetus.

Combined Use of Haloperidol and Lithium

An encephalopathic syndrome (characterized by weakness, lethargy, fever, tremulousness and confusion, extrapyramidal symptoms, leukocytosis, elevated serum enzymes, BUN, and fasting blood sugar) followed by irreversible brain damage has occurred in a few patients treated with lithium plus haloperidol. A causal relationship between these events and the concomitant administration of lithium and haloperidol has not been established; however, patients receiving such combined therapy should be monitored closely for early evidence of neurological toxicity and treatment discontinued promptly if such signs appear.

General

A number of cases of bronchopneumonia, some fatal, have followed the use of antipsychotic drugs, including haloperidol. It has been postulated that lethargy and decreased sensation of thirst due to central inhibition may lead to dehydration, hemoconcentration and reduced pulmonary ventilation. Therefore, if the above signs and symptoms appear, especially in the elderly, the physician should institute remedial therapy promptly.

Although not reported with haloperidol, decreased serum cholesterol and/or cutaneous and ocular changes have been reported in patients receiving chemically-related drugs.

PRECAUTIONS

Leukopenia, Neutropenia, and Agranulocytosis

Class Effect: In clinical trial and/or postmarketing experience, events of leukopenia/neutropenia have been reported temporally related to antipsychotic agents, including haloperidol. Agranulocytosis has also been reported.

Possible risk factors for leukopenia/neutropenia include pre-existing low white blood cell count (WBC) and history of drug-induced leukopenia/neutropenia. Patients with a history of a clinically significant low WBC or a drug-induced leukopenia/neutropenia should have their complete blood count (CBC) monitored frequently during the first few months of therapy and discontinuation of haloperidol should be considered at the first sign of a clinically significant decline in WBC in the absence of other causative factors.

Patients with clinically significant neutropenia should be carefully monitored for fever or other symptoms or signs of infection and treated promptly if such symptoms or signs occur. Patients with severe neutropenia (absolute neutrophil count <1000/mm3) should discontinue haloperidol and have their WBC followed until recovery.

Other

Haloperidol injection should be administered cautiously to patients:

with severe cardiovascular disorders, because of the possibility of transient hypotension and/or precipitation of anginal pain. Should hypotension occur and a vasopressor be required, epinephrine should not be used since haloperidol may block its vasopressor activity and paradoxical further lowering of the blood pressure may occur. Instead, metaraminol, phenylephrine or norepinephrine should be used.
receiving anticonvulsant medications, with a history of seizures, or with EEG abnormalities, because haloperidol may lower the convulsive threshold. If indicated, adequate anticonvulsant therapy should be concomitantly maintained.
with known allergies, or with a history of allergic reactions to drugs.
receiving anticoagulants, since an isolated instance of interference occurred with the effects of one anticoagulant (phenindione).

When haloperidol is used to control mania in cyclic disorders, there may be a rapid mood swing to depression.

Severe neurotoxicity (rigidity, inability to walk or talk) may occur in patients with thyrotoxicosis who are also receiving antipsychotic medication, including haloperidol.

Drug Interactions

Drug-drug interactions can be pharmacodynamic (combined pharmacologic effects) or pharmacokinetic (alteration of plasma levels). The risks of using haloperidol in combination with other drugs have been evaluated as described below.

Pharmacodynamic Interactions

Since QT-prolongation has been observed during haloperidol treatment, caution is advised when prescribing to a patient with QT-prolongation conditions (long QT-syndrome, hypokalemia, electrolyte imbalance) or to patients receiving medications known to prolong the QT-interval or known to cause electrolyte imbalance.

If concomitant antiparkinson medication is required, it may have to be continued after haloperidol is discontinued because of the difference in excretion rates. If both are discontinued simultaneously, extrapyramidal symptoms may occur. The physician should keep in mind the possible increase in intraocular pressure when anticholinergic drugs, including antiparkinson agents, are administered concomitantly with haloperidol.

As with other antipsychotic agents, it should be noted that haloperidol may be capable of potentiating CNS depressants such as anesthetics, opiates and alcohol.

Ketoconazole is a potent inhibitor of CYP3A4. Increases in QTc have been observed when haloperidol was given in combination with the metabolic inhibitors ketoconazole (400 mg/day) and paroxetine (20 mg/day). It may be necessary to reduce the haloperidol dosage.

Pharmacokinetic Interactions

The Effect of Other Drugs on Haloperidol

Haloperidol is metabolized by several routes, including the glucuronidation and the cytochrome P450 enzyme system. Inhibition of these routes of metabolism by another drug may result in increased haloperidol concentrations and potentially increase the risk of certain adverse events, including QT-prolongation.

Drugs Characterized as Substrates, Inhibitors or Inducers of CYP3A4, CYP2D6 or Glucuronidation

In pharmacokinetic studies, mild to moderately increased haloperidol concentrations have been reported when haloperidol was given concomitantly with drugs characterized as substrates or inhibitors of CYP3A4 or CYP2D6 isoenzymes, such as itraconazole, nefazodone, buspirone, venlafaxine, alprazolam, fluvoxamine, quinidine, fluoxetine, sertraline, chlorpromazine, and promethazine.

When prolonged treatment (1 to 2 weeks) with enzyme-inducing drugs such as rifampin or carbamazepine is added to haloperidol therapy, this results in a significant reduction of haloperidol plasma levels.

Rifampin

In a study of 12 schizophrenic patients coadministered oral haloperidol and rifampin, plasma haloperidol levels were decreased by a mean of 70% and mean scores on the Brief Psychiatric Rating Scale were increased from baseline. In 5 other schizophrenic patients treated with haloperidol and rifampin, discontinuation of rifampin produced a mean 3.3-fold increase in haloperidol concentrations.

Carbamazepine

In a study in 11 schizophrenic patients co-administered haloperidol and increasing doses of carbamazepine, haloperidol plasma concentrations decreased linearly with increasing carbamazepine concentrations.

Thus, careful monitoring of clinical status is warranted when enzyme inducing drugs such as rifampin or carbamazepine are administered or discontinued in haloperidol-treated patients. During combination treatment, the haloperidol dose should be adjusted, when necessary. After discontinuation of such drugs, it may be necessary to reduce the dosage of haloperidol.

Valproate

Sodium valproate, a drug known to inhibit glucuronidation, does not affect haloperidol plasma concentrations.

Information for Patients

Haloperidol may impair the mental and/or physical abilities required for the performance of hazardous tasks such as operating machinery or driving a motor vehicle. The ambulatory patient should be warned accordingly.

The use of alcohol with this drug should be avoided due to possible additive effects and hypotension.

Carcinogenesis, Mutagenesis, Impairment of Fertility

No mutagenic potential of haloperidol was found in the Ames Salmonella microsomal activation assay. Negative or inconsistent positive findings have been obtained in in vitro and in vivo studies of effects of haloperidol on chromosome structure and number. The available cytogenetic evidence is considered too inconsistent to be conclusive at this time.

Carcinogenicity studies using oral haloperidol were conducted in Wistar rats (dosed at up to 5 mg/kg daily for 24 months) and in Albino Swiss mice (dosed at up to 5 mg/kg daily for 18 months). In the rat study survival was less than optimal in all dose groups, reducing the number of rats at risk for developing tumors. However, although a relatively greater number of rats survived to the end of the study in high-dose male and female groups, these animals did not have a greater incidence of tumors than control animals. Therefore, although not optimal, this study does suggest the absence of a haloperidol related increase in the incidence of neoplasia in rats at doses up to 20 times the usual daily human dose for chronic or resistant patients.

In female mice at 5 and 20 times the highest initial daily dose for chronic or resistant patients, there was a statistically significant increase in mammary gland neoplasia and total tumor incidence; at 20 times the same daily dose there was a statistically significant increase in pituitary gland neoplasia. In male mice, no statistically significant differences in incidences of total tumors or specific tumor types were noted.

Antipsychotic drugs elevate prolactin levels; the elevation persists during chronic administration. Tissue culture experiments indicate that approximately one-third of human breast cancers are prolactin dependent in vitro, a factor of potential importance if the prescription of these drugs is contemplated in a patient with a previously detected breast cancer. Although disturbances such as galactorrhea, amenorrhea, gynecomastia, and impotence have been reported, the clinical significance of elevated serum prolactin levels is unknown for most patients. An increase in mammary neoplasms has been found in rodents after chronic administration of antipsychotic drugs. Neither clinical studies nor epidemiologic studies conducted to date, however, have shown an association between chronic administration of these drugs and mammary tumorigenesis; the available evidence is considered too limited to be conclusive at this time.

There are no well controlled studies with haloperidol injection in pregnant women. There are reports, however, of cases of limb malformations observed following maternal use of haloperidol along with other drugs which have suspected teratogenic potential during the first trimester of pregnancy. Causal relationships were not established in these cases. Since such experience does not exclude the possibility of fetal damage due to haloperidol, this drug should be used during pregnancy or in women likely to become pregnant only if the benefit clearly justifies a potential risk to the fetus.

Nursing Mothers

Since haloperidol is excreted in human breast milk, infants should not be nursed during drug treatment with haloperidol.

Pediatric Use

Safety and effectiveness in pediatric patients have not been established.

Geriatric Use

Clinical studies of haloperidol did not include sufficient numbers of subjects aged 65 and over to determine whether they respond differently from younger subjects. Other reported clinical experience has not consistently identified differences in responses between the elderly and younger patients. However, the prevalence of tardive dyskinesia appears to be highest among the elderly, especially elderly women (see WARNINGS, TARDIVE DYSKINESIA). Also, the pharmacokinetics of haloperidol in geriatric patients generally warrants the use of lower doses (see DOSAGE AND ADMINISTRATION).

ADVERSE REACTIONS

The following adverse reactions are discussed in more detail in other sections of the labeling:

WARNINGS, Increased mortality in Elderly Patients with Dementia-Related Psychosis
WARNINGS, Cardiovascular Effects
WARNINGS, Tardive Dyskinesia
WARNINGS, Neuroleptic Malignant Syndrome
WARNINGS, Treatment Withdrawal
WARNINGS, Falls
WARNINGS, Usage in Pregnancy
WARNINGS, Combined Use of Haloperidol injection and Lithium
WARNINGS, General
PRECAUTIONS, Leukopenia, Neutropenia, and Agranulocytosis
PRECAUTIONS, Other

Clinical Trials Experience
Because clinical trials are conducted under widely varying conditions, adverse reaction rates observed in the clinical trials of a drug cannot be directly compared to rates in the clinical trials of another drug, and may not reflect the rates observed in practice.

The data described below reflect exposure to haloperidol in the following:

284 patients who participated in 3 double-blind, placebo-controlled clinical trials with haloperidol (oral formulation, 2 to 20 mg/day); two trials were in the treatment of schizophrenia and one in the treatment of bipolar disorder.
1295 patients who participated in 16 double-blind, active comparator-controlled clinical trials with haloperidol (injection or oral formulation, 1 to 45 mg/day) in the treatment of schizophrenia.

Based on the pooled safety data, the most common adverse reactions in haloperidol-treated patients from these double-blind placebo-controlled clinical trials (≥5%) were: extrapyramidal disorder, hyperkinesia, tremor, hypertonia, dystonia, and somnolence.
Adverse Reactions Reported at ≥1% Incidence in Double-Blind Placebo-Controlled Clinical Trials with Oral Haloperidol
Adverse reactions occurring in ≥1% of haloperidol-treated patients and at higher rate than placebo in 3 double-blind, parallel, placebo-controlled, clinical trials with the oral formulation are shown in Table 1.

Additional Adverse Reactions Reported in Double-Blind, Placebo- or Active Comparator-Controlled Clinical Trials with Injectable or Oral Haloperidol
Additional adverse reactions that are listed below were reported by haloperidol-treated patients in double-blind, active comparator-controlled clinical trials with the injectable or oral formulation, or at <1% incidence in double-blind, parallel, placebo-controlled, clinical trials with the oral formulation.
Cardiac Disorders: Tachycardia
Endocrine Disorders: Hyperprolactinemia
Eye Disorders: Vision blurred
Investigations: Weight Increased
Musculoskeletal and Connective Tissue Disorders: Torticollis, Trismus, Muscle rigidity, Muscle twitching
Nervous System Disorders: Akathisia, Dizziness, Dyskinesia, Hypokinesia, Neuroleptic malignant syndrome, Nystagmus, Oculogyric crisis, Parkinsonism, Sedation, Tardive dyskinesia
Psychiatric Disorders: Loss of libido, Restlessness
Reproductive System and Breast Disorders: Amenorrhea, Galactorrhea, Dysmenorrhea, Erectile dysfunction, Menorrhagia, Breast discomfort
Skin and Subcutaneous Tissue Disorders: Acneiform skin reactions
Vascular Disorders: Hypotension, Orthostatic hypotension
Postmarketing Experience

The following adverse reactions relating to the active moiety haloperidol have been identified during postapproval use of haloperidol or haloperidol decanoate. Because these reactions are reported voluntarily from a population of uncertain size, it is not always possible to reliably estimate their frequency or establish a causal relationship to drug exposure.
Blood and Lymphatic System Disorders: Pancytopenia, Agranulocytosis, Thrombocytopenia,

Leukopenia, Neutropenia
Cardiac Disorders: Ventricular fibrillation, Torsade de pointes, Ventricular tachycardia,

Extrasystoles

Endocrine Disorders: Inappropriate antidiuretic hormone secretion
Gastrointestinal Disorders: Vomiting, Nausea
General Disorders and Administration Site Conditions: Sudden death, Face edema,

Edema, Hyperthermia, Hypothermia
Hepatobiliary Disorders: Acute hepatic failure, Hepatitis, Cholestasis, Jaundice, Liver

function test abnormal
Immune System Disorders: Anaphylactic reaction, Hypersensitivity
Investigations: Electrocardiogram QT prolonged, Weight decreased
Metabolic and Nutritional Disorders: Hypoglycemia
Musculoskeletal and Connective Tissue Disorders: Rhabdomyolysis
Nervous System Disorders: Convulsion, Headache, Opisthotonus, Tardive dystonia
Pregnancy, Puerperium and Perinatal Conditions: Drug withdrawal syndrome neonatal
Psychiatric Disorders: Agitation, Confusional state, Depression, Insomnia
Renal and Urinary Disorders: Urinary retention
Reproductive System and Breast Disorders: Priapism, Gynecomastia
Respiratory, Thoracic and Mediastinal Disorders: Laryngeal edema, Bronchospasm,

Laryngospasm, Dyspnea
Skin and Subcutaneous Tissue Disorders: Dermatitis exfoliative, Hypersensitivity

vasculitis, Photosensitivity reaction, Urticaria, Pruritis, Rash, Hyperhidrosis

OVERDOSAGE

Manifestations

In general, the symptoms of overdosage would be an exaggeration of known pharmacologic effects and adverse reactions, the most prominent of which would be: 1) severe extrapyramidal reactions, 2) hypotension, or 3) sedation. The patient would appear comatose with respiratory depression and hypotension which could be severe enough to produce a shocklike state. The extrapyramidal reactions would be manifested by muscular weakness or rigidity and a generalized or localized tremor as demonstrated by the akinetic or agitans types respectively. With accidental overdosage, hypertension rather than hypotension occurred in a two-year old child. The risk of ECG changes associated with Torsades de Pointes should be considered. (For further information regarding Torsades de Pointes, please refer to A ADVERSE REACTIONS).

Treatment

Since there is no specific antidote, treatment is primarily supportive. A patent airway must be established by use of an oropharyngeal airway or endotracheal tube or, in prolonged cases of coma, by tracheostomy. Respiratory depression may be counteracted by artificial respiration and mechanical respirators. Hypotension and circulatory collapse may be counteracted by use of intravenous fluids, plasma, or concentrated albumin, and vasopressor agents such as metaraminol, phenylephrine and norepinephrine. Epinephrine should not be used. In case of severe extrapyramidal reactions, antiparkinson medication should be administered. ECG and vital signs should be monitored especially for signs of QT-prolongation or dysrhythmias and monitoring should continue until the ECG is normal. Severe arrhythmias should be treated with appropriate antiarrhythmic measures.

DOSAGE & ADMINISTRATION

There is considerable variation from patient to patient in the amount of medication required for treatment. As with all drugs used to treat schizophrenia, dosage should be individualized according to the needs and response of each patient. Dosage adjustments, either upward or downward, should be carried out as rapidly as practicable to achieve optimum therapeutic control.

To determine the initial dosage, consideration should be given to the patient’s age, severity of illness, previous response to other antipsychotic drugs, and any concomitant medication or disease state. Debilitated or geriatric patients, as well as those with a history of adverse reactions to antipsychotic drugs, may require less haloperidol injection. The optimal response in such patients is usually obtained with more gradual dosage adjustments and at lower dosage levels.

Parenteral medication, administered intramuscularly in doses of 2 to 5 mg, is utilized for prompt control of the acutely agitated schizophrenic patient with moderately severe to very severe symptoms. Depending on the response of the patient, subsequent doses may be given, administered as often as every hour, although 4 to 8 hour intervals may be satisfactory. The maximum dose is 20 mg/day.

Controlled trials to establish the safety and effectiveness of intramuscular administration in children have not been conducted.

Parenteral drug products should be inspected visually for particulate matter and discoloration prior to administration, whenever solution and container permit.

Switchover Procedure

An oral form should supplant the injectable as soon as practicable. In the absence of bioavailability studies establishing bioequivalence between these two dosage forms the following guidelines for dosage are suggested. For an initial approximation of the total daily dose required, the parenteral dose administered in the preceding 24 hours may be used. Since this dose is only an initial estimate, it is recommended that careful monitoring of clinical signs and symptoms, including clinical efficacy, sedation, and adverse effects, be carried out periodically for the first several days following the initiation of switchover. In this way, dosage adjustments, either upward or downward, can be quickly accomplished. Depending on the patient’s clinical status, the first oral dose should be given within 12 to 24 hours following the last parenteral dose.

HOW SUPPLIED

Haloperidol Injection, USP is supplied as follows:

Store at 20° to 25°C (68° to 77°F) [see USP Controlled Room Temperature]. Do not freeze.

PROTECT FROM LIGHT.

The container closure is not made with natural rubber latex.

SPL UNCLASSIFIED

Lake Zurich, IL 60047
www.fresenius-kabi.com/us
45850L
Revised: March 2019

PRINCIPAL DISPLAY PANEL - NDC 51662-1524-1 VIAL LABELING

PACKAGE LABEL - PRINCIPAL DISPLAY - Haloperidol Injection 1 mL Vial Label

Haloperidol
Injection, USP
(For Immediate Release)

5 mg per mL

For intramuscular use.
Sterile. Project from light.

1 mL Single Dose Vial Rx only